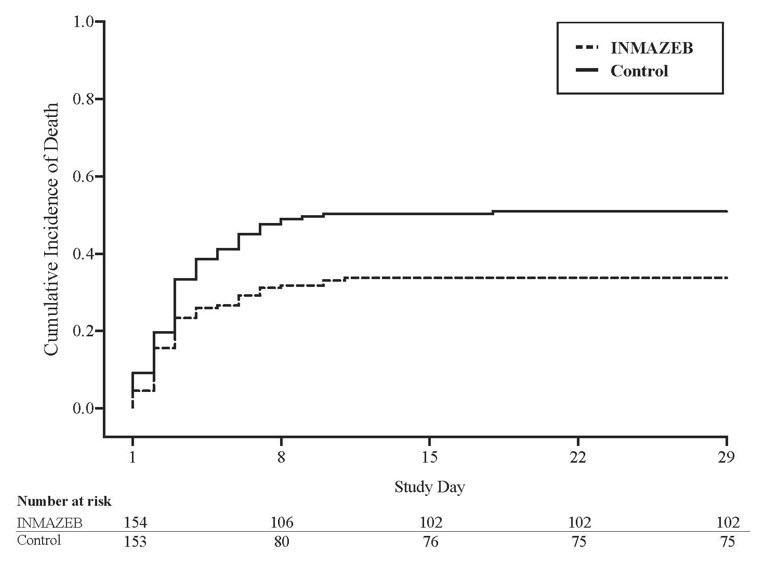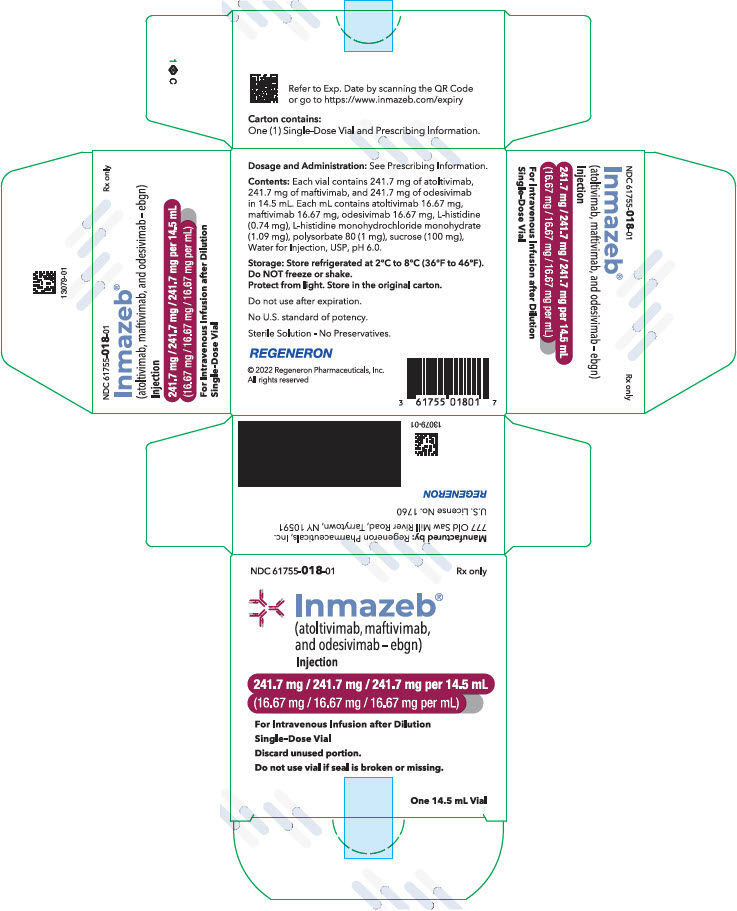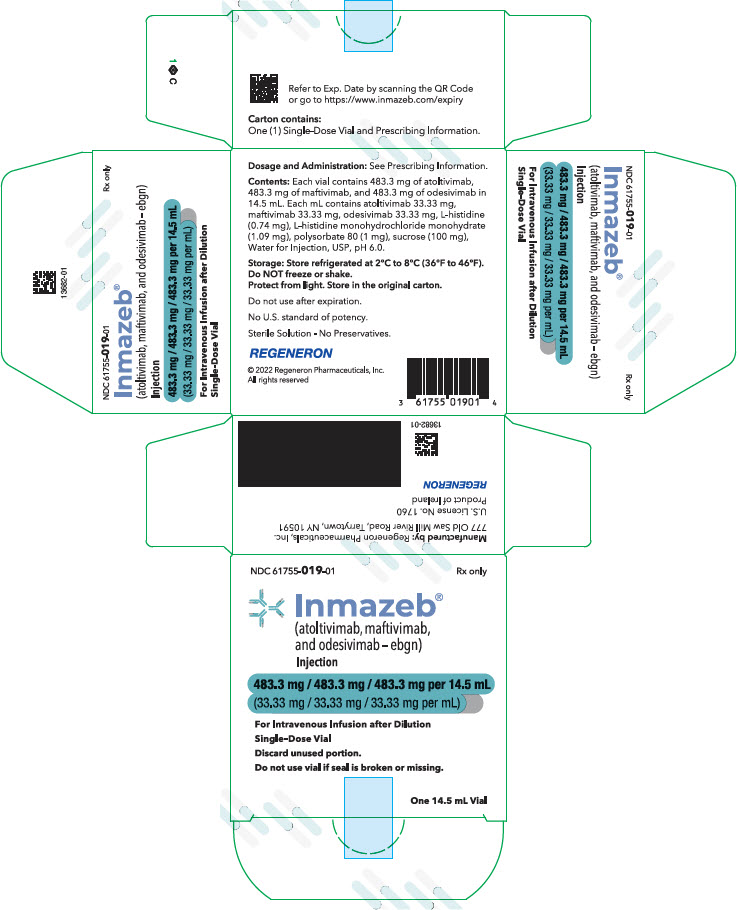 DRUG LABEL: Inmazeb
NDC: 61755-018 | Form: INJECTION, SOLUTION
Manufacturer: Regeneron Pharmaceuticals, Inc.
Category: prescription | Type: HUMAN PRESCRIPTION DRUG LABEL
Date: 20251215

ACTIVE INGREDIENTS: atoltivimab 241.7 mg/14.5 mL; maftivimab 241.7 mg/14.5 mL; odesivimab 241.7 mg/14.5 mL
INACTIVE INGREDIENTS: HISTIDINE; HISTIDINE MONOHYDROCHLORIDE MONOHYDRATE; Polysorbate 80; Sucrose; Water

HIGHLIGHTS OF PRESCRIBING INFORMATION

These highlights do not include all the information needed to use INMAZEB safely and effectively. See full prescribing information for INMAZEB.
INMAZEB® (atoltivimab, maftivimab, and odesivimab-ebgn) injection, for intravenous use
Initial U.S. Approval: 2020

1 INDICATIONS AND USAGE

INMAZEB is a combination of Orthoebolavirus zairense glycoprotein-directed human monoclonal antibodies (atoltivimab, maftivimab, and odesivimab), indicated for the treatment of infection caused by Orthoebolavirus zairense in adult and pediatric patients, including neonates born to a mother who is RT-PCR positive for Orthoebolavirus zairense infection. (1)

Limitation of Use

- The efficacy of INMAZEB has not been established for other species of the Orthoebolavirus and Orthomarburgvirus genera.
- Orthoebolavirus zairense can change over time, and factors such as emergence of resistance, or changes in viral virulence could diminish the clinical benefit of antiviral drugs. Consider available information on drug susceptibility patterns for circulating Orthoebolavirus zairense strains when deciding whether to use INMAZEB.

2 DOSAGE AND ADMINISTRATION

The recommended dosage of INMAZEB is 50 mg of atoltivimab, 50 mg of maftivimab, and 50 mg of odesivimab per kg diluted and administered as a single intravenous infusion. (2.1)

Refer to the Full Prescribing Information for information on preparation and administration. (2.2)

3 DOSAGE FORMS AND STRENGTHS

Injection:

- 241.7 mg of atoltivimab, 241.7 mg of maftivimab, and 241.7 mg of odesivimab per 14.5 mL (16.67 mg/16.67 mg/16.67 mg per mL) in a single-dose vial. (3)
- 483.3 mg of atoltivimab, 483.3 mg of maftivimab, and 483.3 mg of odesivimab per 14.5 mL (33.33 mg/33.33 mg/33.33 mg per mL) in a single-dose vial. (3)

4 CONTRAINDICATIONS

None. (4)

5 WARNINGS AND PRECAUTIONS

Hypersensitivity Reactions Including Infusion-Associated Events: Hypersensitivity reactions including infusion-associated events have been reported during and post-infusion with INMAZEB. These may include acute, life-threatening reactions during and after the infusion. Monitor patients and in the case of severe or life-threatening hypersensitivity reactions, discontinue the administration of INMAZEB immediately and administer appropriate emergency care. (5.1)

6 ADVERSE REACTIONS

The most common adverse events (incidence ≥20%) were pyrexia, chills, tachycardia, tachypnea, and vomiting. (6.1)

To report SUSPECTED ADVERSE REACTIONS, contact Regeneron at 1-844-734-6643 or www.regeneron.com/contact or FDA AT 1-800-FDA-1088 or www.fda.gov/medwatch.

7 DRUG INTERACTIONS

Interaction with live vaccine indicated for prevention of Orthoebolavirus zairense infection: No vaccine interaction studies have been performed. INMAZEB may reduce the efficacy of the live vaccine. The interval between live vaccination following initiation of INMAZEB therapy should be in accordance with current vaccination guidelines. (7.1)

8 USE IN SPECIFIC POPULATIONS

Lactation: Patients infected with Orthoebolavirus zairense should be instructed not to breastfeed due to the potential for Orthoebolavirus zairense transmission. (8.2)

FULL PRESCRIBING INFORMATION

1 INDICATIONS AND USAGE

INMAZEB is indicated for the treatment of infection caused by Orthoebolavirus zairense in adult and pediatric patients, including neonates born to a mother who is RT-PCR positive for Orthoebolavirus zairense infection [see Dosage and Administration (2.2), and Clinical Studies (14)].

Limitations of Use

The efficacy of INMAZEB has not been established for other species of the Orthoebolavirus and Orthomarburgvirus genera.

Orthoebolavirus zairense can change over time, and factors such as emergence of resistance, or changes in viral virulence could diminish the clinical benefit of antiviral drugs. Consider available information on drug susceptibility patterns for circulating Orthoebolavirus zairense strains when deciding whether to use INMAZEB.

2 DOSAGE AND ADMINISTRATION

2.1 Recommended Dosage

INMAZEB is a combination of three human monoclonal antibodies co-formulated in a 1:1:1 ratio of atoltivimab, maftivimab, and odesivimab. INMAZEB is available as two different strength presentations, containing either 16.67 mg of each antibody per mL or 33.33 mg of each antibody per mL [see Dosage Forms and Strengths (3)].

The recommended dosage of INMAZEB is 50 mg of atoltivimab, 50 mg of maftivimab, and 50 mg of odesivimab per kg diluted and administered as a single intravenous infusion as shown in Table 1 [see Dosage and Administration (2.2)].

2.2 Preparation and Administration

INMAZEB must be prepared and administered under the supervision of a healthcare provider. Parenteral drug products should be inspected visually for particulate matter and discoloration prior to administration, whenever solution and container permit. INMAZEB should be clear to slightly opalescent, colorless to pale yellow solution that is free from visible particulates. Discard the vial if the solution is cloudy, discolored or contains particulate matter.

Preparation for Intravenous Infusion

- The recommended dosage is based on 50 mg of atoltivimab, 50 mg of maftivimab, and 50 mg of odesivimab per kg. For example, a patient weighing 50 kg the recommended dosage is 2,500 mg of atoltivimab, 2,500 mg of maftivimab, and 2,500 mg of odesivimab.
- Determine the number of vials needed based on the calculated dose in volume (mL).
  - The number of vials needed depends on the INMAZEB strength used. Refer to Table 1 for the corresponding volume per kg needed to withdraw from each available strength presentation to prepare dose.
  - Multiple INMAZEB vials may be needed. Each vial contains 14.5 mL of INMAZEB solution, regardless of the strength presentation. For example, for a 50 kg patient, the volume of INMAZEB needed is 150 mL (11 vials) if using the 16.67 mg/16.67 mg/16.67 mg per mL solution or 75 mL (6 vials) if using the 33.33 mg/33.33 mg/33.33 mg per mL solution.

Table 1: INMAZEB Dosage (Volume per kg) for Intravenous Infusion Preparation
When Using the | When Using the
241.7 mg of atoltivimab, 241.7 mg of maftivimab, and 241.7 mg of odesivimab per 14.5 mL | 483.3 mg of atoltivimab, 483.3 mg of maftivimab, and 483.3 mg of odesivimab per 14.5 mL
(16.67 mg /16.67 mg /16.67 mg per mL) Solution | (33.33 mg/33.33 mg /33.33 mg per mL) Solution
Withdraw 3 mL of solution per kg to prepare the dose | Withdraw 1.5 mL of solution per kg to prepare the dose

- Do not shake the vial.
- Prior to intravenous infusion, INMAZEB must be further diluted in an intravenous PVC infusion bag containing either 0.9% Sodium Chloride Injection, USP, 5% Dextrose Injection, USP, or Lactated Ringer's Injection, USP. For neonates, the INMAZEB solution should be diluted in 5% Dextrose Injection, USP (see Table 2). The total volume of the infusion solution to be administered is based on the patient's body weight and is specified in Table 2.
- Select a diluent solution infusion bag of appropriate fill volume based on the patient's body weight (see Table 2). Withdraw and discard from the bag a volume of diluent solution equal to the calculated dose in volume (mL) of INMAZEB. Then add the calculated volume of INMAZEB to the bag. For example:
  - When using the 16.67 mg/16.67 mg/16.67 mg per mL solution for a 50 kg patient, withdraw and discard 150 mL of diluent from a 500 mL infusion bag. Then add 150 mL of INMAZEB to obtain a total infusion volume of 500 mL.
  - When using the 33.33 mg/33.33 mg/33.33 mg per mL solution for a 50 kg patient, withdraw and discard 75 mL of diluent from a 500 mL infusion bag. Then add 75 mL of INMAZEB to obtain a total infusion volume of 500 mL.

Table 2: INMAZEB Infusion Volumes and Times by Body Weight
Body Weight (kg) | Total Infusion Volume After Dilution (mL) [The recommended infusion volume ensures the final concentration of the diluted solution is 9.5 mg/mL to 23.7 mg/mL for the 16.67 mg/16.67 mg/16.67 mg per mL solution and 9.5 mg/mL to 30 mg/mL for the 33.33 mg/33.33 mg/33.33 mg per mL solution. 5% Dextrose Injection, USP is recommended for neonates.] | Infusion Time
0.5 to less than 1 | 7 | 4 hours
1 to 1.9 | 15
2 to 3.9 | 25 | 3 hours
4 to 7 | 50 | 3 hours
8 to 15 | 100 | 3 hours
16 to 38 | 250 | 2 hours
39 to 79 | 500 | 2 hours
80 to 149 | 1,000 | 2 hours
150 and above | 2,000 | 4 hours

- Mix the diluted solution by gentle inversion. Do not shake.
- INMAZEB does not contain preservatives. It is always recommended to administer intravenous medication immediately after preparation when possible. Store the diluted INMAZEB solution as specified in Table 3.
- Do not freeze the diluted solution.
- Discard any unused medicinal product or waste material.

Table 3: Diluted INMAZEB Solution Storage Conditions
Diluent Used to Prepare Solution for Infusion | Diluted INMAZEB Solution Storage Conditions
0.9% Sodium Chloride Injection, USP | Store at room temperature up to 25°C (77°F) for no more than 8 hours or refrigerated at 2°C to 8°C (36°F to 46°F) for no more than 24 hours.
5% Dextrose Injection, USP | Store at room temperature up to 25°C (77°F) for no more than 4 hours or refrigerated at 2°C to 8°C (36°F to 46°F) for no more than 24 hours.
Lactated Ringer's Injection, USP | Store at room temperature up to 25°C (77°F) for no more than 4 hours or refrigerated at 2°C to 8°C (36°F to 46°F) for no more than 4 hours.

Administration

- INMAZEB must be administered by a healthcare provider.
- Allow the diluted infusion solution to come to room temperature prior to administration.
  - INMAZEB diluted with 5% Dextrose Injection, USP can be infused at temperatures up to 35°C (95°F). When the temperature is higher than 25°C (77°F), administer the diluted INMAZEB with 5% Dextrose Injection, USP immediately after completion of dose preparation.
- Administer the diluted infusion solution intravenously through an intravenous line containing a sterile, in-line or add-on 0.2-micron filter.
- The infusion rate is based on the patient's body weight and prepared infusion volume. Select an appropriate infusion rate for the diluted infusion solution (see Table 2). It is important to follow the infusion time outlined in Table 2 based on the patient's weight.
- The rate of infusion of INMAZEB may be slowed or interrupted if the patient develops any signs of infusion-associated events or other adverse events [see Warnings and Precautions (5.1)].
- Do not mix other medications with INMAZEB.
- Compatibility studies of INMAZEB have not been performed when co-administering other drugs simultaneously through the same infusion line.

3 DOSAGE FORMS AND STRENGTHS

INMAZEB is a clear to slightly opalescent and colorless to pale yellow solution available as:

- Injection: 241.7 mg of atoltivimab, 241.7 mg of maftivimab, and 241.7 mg of odesivimab per 14.5 mL (16.67 mg/16.67 mg/16.67 mg per mL) in a single-dose vial.
- Injection: 483.3 mg of atoltivimab, 483.3 mg of maftivimab, and 483.3 mg of odesivimab per 14.5 mL (33.33 mg/33.33 mg/33.33 mg per mL) in a single-dose vial.

4 CONTRAINDICATIONS

None.

5 WARNINGS AND PRECAUTIONS

5.1 Hypersensitivity Reactions Including Infusion-Associated Events

Hypersensitivity reactions including infusion-associated events have been reported during and post-infusion with INMAZEB. These may include acute, life-threatening reactions during and after the infusion. Monitor all patients for signs and symptoms including, but not limited to, hypotension, chills and elevation of fever, during and following INMAZEB infusion. In the case of severe or life-threatening hypersensitivity reactions, discontinue the administration of INMAZEB immediately and administer appropriate emergency care [see Adverse Reactions (6.1)].

Infusion could not be completed in 1% of subjects who received INMAZEB due to infusion-associated adverse events. The rate of infusion of INMAZEB may be slowed or interrupted if the patient develops any signs of infusion-associated events or other adverse events [see Adverse Reactions (6.1)].

6 ADVERSE REACTIONS

The following clinically significant adverse reactions are described elsewhere in the labeling:

- Hypersensitivity Reactions Including Infusion-Associated Events [see Warnings and Precautions (5.1)]

6.1 Clinical Trials Experience

Because clinical trials are conducted under widely varying conditions, adverse reaction rates may not reflect the rates observed in practice.

Overall, 382 adult and pediatric subjects with Orthoebolavirus zairense infection received INMAZEB in one clinical trial (the PALM trial) and as part of an expanded access program conducted in the Democratic Republic of Congo during a Orthoebolavirus zairense outbreak in 2018-2019. In the PALM trial, the safety of INMAZEB was evaluated in a multi-center, open-label, randomized controlled trial, in which 154 subjects (115 adult subjects and 39 pediatric subjects) received INMAZEB [50 mg of atoltivimab, 50 mg of maftivimab, and 50 mg of odesivimab per kg (3 mL/kg)] intravenously as a single infusion and 168 subjects received an investigational control [see Clinical Studies (14)]. All subjects received optimized standard of care treatment. During the same outbreak, INMAZEB [50 mg of atoltivimab, 50 mg of maftivimab, and 50 mg of odesivimab per kg (3 mL/kg)] was given to 228 subjects (190 adult subjects and 38 pediatric subjects) in the expanded access program.

The safety data described below is derived from the PALM trial.

Table 4 summarizes adverse events that were reported during INMAZEB infusion. The evaluation of adverse events in subjects who received INMAZEB may have been confounded by the signs and symptoms of the underlying Orthoebolavirus zairense infection. The most common adverse events reported in at least 20% of subjects who received INMAZEB were pyrexia (or elevation in fever), chills, tachycardia, tachypnea, and vomiting. The adverse event profile in adult and pediatric subjects treated with INMAZEB was similar.

Table 4: Adverse Events That Occurred during INMAZEB Infusion in ≥10% of Adult and Pediatric Subjects in the PALM Trial
Adverse Event [Adverse events in this table were reported as preferred terms from a list of pre-defined or other adverse events that occurred on the day of infusion, and included signs and symptoms that occurred during or immediately after infusion] | INMAZEB (N=154) % | Control [Investigational therapy administered as three separate infusions] (N=168) %
Pyrexia (Elevation in fever) | 54 | 58
Chills | 39 | 33
Tachycardia | 20 | 32
Tachypnea | 19 | 28
Vomiting [Adverse events that were not pre-specified] | 19 | 23
Hypotension | 15 | 31
Diarrhea | 11 | 18
Hypoxia | 10 | 11

The following pre-specified symptoms, which were assessed on a daily basis while admitted to the treatment unit, were reported in 40% or more of subjects who received INMAZEB: diarrhea, pyrexia, and vomiting. Evaluation of these symptoms may have been confounded by the underlying Orthoebolavirus zairense infection.

Discontinuation and Infusion Rate Adjustments in the PALM Trial

Approximately 99% of subjects who received INMAZEB in the PALM trial were able to complete their dose within three hours. Two subjects who received INMAZEB (1%) did not receive their complete infusion. One of the two subjects did not complete their INMAZEB infusion because of fever elevation [see Warnings and Precautions (5.1)].

Selected Laboratory Abnormalities in the PALM Trial

Table 5 presents selected laboratory abnormalities (worsening to Grade 3 or 4 compared to baseline) for adult and pediatric subjects in the PALM trial.

Table 5: Selected Grade 3 and 4 Laboratory Abnormalities, Worsened Grade from Baseline for Adult and Pediatric Subjects in the PALM Trial
Laboratory Test [Graded per Division of AIDS (DAIDS) v2.1] | INMAZEB N=154 % | Control N=168 %
Sodium, high ≥ 154 mmol/L | 9 | 4
Sodium, low < 125 mmol/L | 7 | 11
Potassium, high ≥ 6.5 mmol/L | 13 | 12
Potassium, low < 2.5 mmol/L | 9 | 8
Creatinine (mg/dL) ≥ 1.8 × ULN [ULN for creatinine was 1.2 mg/dL. Criterion for increase to ≥ 1.5 × from baseline was applied if the worsening grade was higher.] | 15 | 23
Alanine aminotransferase (U/L) ≥ 5 × ULN | 10 | 14
Aspartate aminotransferase (U/L) ≥ 5 × ULN | 21 | 18
ULN = upper limit of normal

6.2 Immunogenicity

As with all therapeutic proteins, there is potential for immunogenicity. The detection of antibody formation is highly dependent on the sensitivity and specificity of the assay. Additionally, the observed incidence of antibody (including neutralizing antibody) positivity in an assay may be influenced by several factors including assay methodology, sample handling, timing of sample collection, concomitant medications, and underlying disease. For these reasons, comparison of the incidence of antibodies in the study described below with the incidence of antibodies in other studies or to other atoltivimab, maftivimab, and odesivimab products may be misleading.

The development of anti-atoltivimab, anti-maftivimab, and anti-odesivimab antibodies was evaluated in 24 healthy adults in a single dose, randomized, double-blind, placebo-controlled, dose escalation study. Immunogenic responses against atoltivimab, maftivimab, and odesivimab were not detected at baseline or through 168 days post-dose in any subjects.

7 DRUG INTERACTIONS

7.1 Vaccine Interactions

No vaccine-therapeutic interaction studies have been performed in human subjects using INMAZEB. However, because of the potential for INMAZEB to inhibit replication of a live vaccine virus indicated for prevention of Orthoebolavirus zairense infection and possibly reduce the efficacy of the vaccine, avoid the concurrent administration of a live vaccine during treatment with INMAZEB. The interval between live vaccination following initiation of INMAZEB therapy should be in accordance with current vaccination guidelines. The efficacy of INMAZEB among subjects who reported receipt of a recombinant live vaccine prior to their enrollment in the PALM clinical trial was similar to subjects who did not receive a vaccine.

8 USE IN SPECIFIC POPULATIONS

8.1 Pregnancy

Risk Summary

Orthoebolavirus zairense infection is life-threatening for both the mother and fetus and treatment should not be withheld due to pregnancy (see Clinical Considerations). Available data from the PALM trial and an expanded access program in which pregnant women with Orthoebolavirus zairense infection were treated with INMAZEB demonstrate the high rate of maternal and fetal/neonatal morbidity consistent with published literature regarding the risk associated with underlying maternal Orthoebolavirus zairense infection. These data are insufficient to evaluate for a drug-associated risk of major birth defects, miscarriage, or adverse maternal/fetal outcome. Animal reproduction studies with INMAZEB have not been conducted. Human monoclonal antibodies, such as INMAZEB, are transported across the placenta; therefore, INMAZEB has the potential to be transferred from the mother to the developing fetus.

Clinical Considerations

Disease-associated maternal and/or embryo/fetal risk

Maternal, fetal and neonatal outcomes are poor among pregnant women infected with Orthoebolavirus zairense. The majority of such pregnancies result in maternal death with miscarriage, stillbirth, or neonatal death. Treatment should not be withheld due to pregnancy.

8.2 Lactation

Risk Summary

The Centers for Disease Control and Prevention recommend that patients with confirmed Orthoebolavirus zairense not breastfeed their infants to reduce the risk of postnatal transmission of Orthoebolavirus zairense infection.

There are no data on the presence of atoltivimab, maftivimab, and odesivimab-ebgn in human or animal milk, the effects on the breastfed infant, or the effects on milk production. Maternal IgG is known to be present in human milk. The effects of local gastrointestinal exposure and limited systemic exposure in the breastfed infant to atoltivimab, maftivimab, or odesivimab-ebgn are unknown.

8.4 Pediatric Use

The safety and effectiveness of INMAZEB for the treatment of infection caused by Orthoebolavirus zairense have been established in pediatric patients from birth to less than 18 years of age. Use of INMAZEB for this indication is supported by evidence from a multi-center, open label, randomized controlled trial of INMAZEB in adults and pediatric subjects that included 39 pediatric subjects birth to less than 18 years of age, including neonates born to a mother who is RT-PCR positive for Orthoebolavirus zairense infection. The 28-day mortality and safety in adult and pediatric subjects treated with INMAZEB were similar [see Adverse Reactions (6.1) and Clinical Studies (14)]. An additional 38 pediatric subjects from birth to less than 18 years of age received INMAZEB in an expanded access program.

8.5 Geriatric Use

Clinical studies of INMAZEB did not include sufficient numbers of subjects aged 65 and over to determine whether they respond differently from younger subjects. Of the 154 subjects with Orthoebolavirus zairense infection who received INMAZEB in the randomized controlled trial, 5 (3.2%) were 65 years or older. The limited clinical experience has not identified differences in responses between the elderly and younger subjects.

11 DESCRIPTION

Atoltivimab, maftivimab, and odesivimab-ebgn is a combination of Orthoebolavirus zairense glycoprotein (GP) directed recombinant human IgG1 human monoclonal antibodies of similar structure. The human monoclonal antibodies, atoltivimab, maftivimab, and odesivimab are produced by recombinant DNA technology in Chinese hamster ovary (CHO) cell suspension culture and have an approximate molecular weight of 145 kDa, 146 kDa and 144 kDa, respectively.

INMAZEB (atoltivimab, maftivimab, and odesivimab-ebgn) injection for intravenous use is a sterile, preservative-free, clear to slightly opalescent, colorless to pale yellow solution, that is free from visible particulates.

INMAZEB injection is supplied as two strength presentations:

- 16.67 mg/16.67 mg/16.67 mg per mL: Each vial contains 241.7 mg of atoltivimab, 241.7 mg of maftivimab, and 241.7 mg of odesivimab in 14.5 mL. Each mL contains 16.67 mg of atoltivimab, 16.67 mg of maftivimab, 16.67 mg of odesivimab, and L-histidine (0.74 mg), L-histidine monohydrochloride monohydrate (1.09 mg), polysorbate 80 (1 mg), sucrose (100 mg), and Water for Injection, USP with a pH of 6.0.
- 33.33 mg/33.33 mg/33.33 mg per mL: Each vial contains 483.3 mg of atoltivimab, 483.3 mg of maftivimab, and 483.3 mg of odesivimab in 14.5 mL. Each mL contains 33.33 mg of atoltivimab, 33.33 mg of maftivimab, 33.33 mg of odesivimab, and L-histidine (0.74 mg), L-histidine monohydrochloride monohydrate (1.09 mg), polysorbate 80 (1 mg), sucrose (100 mg), and Water for Injection, USP with a pH of 6.0.

12 CLINICAL PHARMACOLOGY

12.1 Mechanism of Action

INMAZEB is an antiviral drug combination of three recombinant human IgG1κ monoclonal antibodies (atoltivimab, maftivimab, and odesivimab) that inhibit Orthoebolavirus zairense [see Microbiology (12.4)].

12.2 Pharmacodynamics

Atoltivimab, maftivimab, and odesivimab exposure-response relationships and the time course of pharmacodynamic response are unknown.

12.3 Pharmacokinetics

No pharmacokinetic data are available in patients with Orthoebolavirus zairense infection. The pharmacokinetics of atoltivimab, maftivimab, and odesivimab in 18 healthy subjects 21 to 60 years of age are linear and dose-proportional over the range of 1 mg of atoltivimab, 1 mg of maftivimab, and 1 mg of odesivimab per kg to 50 mg of atoltivimab, 50 mg of maftivimab, and 50 mg of odesivimab per kg (0.02 to 1 times the approved recommended dosage) of INMAZEB following a single intravenous (IV) infusion. Pharmacokinetic parameters for the individual antibodies of INMAZEB are provided in Table 6.

Table 6: Pharmacokinetic Parameters of INMAZEB Administered IV in Healthy Subjects
 | Atoltivimab 50 mg/kg [INMAZEB was administered at a total dose of 50 mg of atoltivimab, 50 mg of maftivimab, and 50 mg of odesivimab per kg in a 1:1:1 ratio.] | Maftivimab 50 mg/kg | Odesivimab 50 mg/kg
Systemic Exposure (n=6)
Mean (SD) Cmax, mg/L | 1,220 (101) | 1,280 (68.0) | 1,260 (81.2)
Mean (SD) AUCinf, mg day/L | 17,100 (4,480) | 18,700 (4,100) | 25,600 (5,040)
Distribution
Mean (SD) Volume of Distribution at Steady State, mL/kg | 58.2 (2.66) | 57.6 (3.89) | 56.0 (3.16)
Elimination
Mean (SD) Elimination Half-Life (days) | 21.2 (3.36) | 22.3 (3.09) | 25.3 (3.86)
Mean (SD) Clearance (mL/day/kg) | 3.08 (0.719) | 2.78 (0.558) | 2.02 (0.374)

Specific Populations

The effect of age (< 21 or > 60), renal impairment, or hepatic impairment on the pharmacokinetics of atoltivimab, maftivimab, and odesivimab is unknown.

12.4 Microbiology

Mechanism of Action

INMAZEB is a combination of three recombinant human IgG1κ monoclonal antibodies each targeting the Orthoebolavirus zairense glycoprotein (EBOV GP). Orthoebolavirus zairense (EBOV) encodes a sole envelope protein, the glycoprotein, which mediates virus attachment and membrane fusion with the host cell membranes. In addition, GP is expressed on the surface of Orthoebolavirus zairense infected host cells making it a target for antibodies that can mediate killing of these cells by antibody dependent cellular cytotoxicity and/or other effector functions. The 3 antibodies that make up the combination bind to 3 non-overlapping epitopes on GP and all 3 antibodies can bind the GP simultaneously. The mean KD values for atoltivimab, maftivimab, and odesivimab were 7.84 nM, 3.34 nM, and 8.26 nM, respectively, as determined by surface plasmon resonance. Maftivimab is a neutralizing antibody that blocks entry of the virus into susceptible cells. Odesivimab is a non-neutralizing antibody that induces antibody-dependent effector function through FcyRIIIa signaling when bound to its target. Odesivimab also binds to the soluble form of Orthoebolavirus zairense glycoprotein (sGP). Atoltivimab combines both neutralization and FcyRIIIa signaling activities.

Antiviral Activity

In a live virus infection assay on Vero cells, maftivimab neutralized Mayinga, Kikwit, and Makona strains of Orthoebolavirus zairense, with a concentration between 0.2 and 1.2 nM (0.03 and 0.18 μg/mL) providing 80% inhibition of viral infection in a plaque-reduction neutralization test (PRNT-80). Atoltivimab and odesivimab did not demonstrate any neutralizing activity in this assay. Effector function activity of INMAZEB individual antibodies was assessed with an EBOV Makona-GP expressing cell line and Jurkat/NFAT-Luc/FcγRIIIa reporter effector cells. The EC50 values of atoltivimab and odesivimab were 2.9 nM and 1.6 nM, respectively, whereas maftivimab did not exhibit any FcγRIIIa signaling activity at the maximum concentration tested, 40 nM.

Treatment of Orthoebolavirus zairense infected rhesus macaques with a single intravenous dose of INMAZEB (50 mg of atoltivimab, 50 mg of maftivimab, and 50 mg of odesivimab per kg) generally protected infected animals from Orthoebolavirus zairense mediated death when drug was administered 5 days post-infection.

Resistance

No clinical data are available on the development of EBOV resistance to INMAZEB. Previously identified substitutions in EBOV were assessed for activity in binding, neutralization and ADCC. Results of these assays are presented in Table 7, Table 8, and Table 9. The clinical significance of these substitutions is unknown.

Binding Activity

Binding was assessed with an electrochemiluminescence (ECL)-based assay using virus like particles (VLPs) pseudotyped with EBOV Makona 2014 reference GP or variant EBOV GP. The results of this assay are shown in Table 7.

Table 7: Summary of Reduced Binding of Atoltivimab, Odesivimab, Maftivimab and INMAZEB to VLPs Pseudotyped with EBOV GP Variants Compared to EBOV Makona 2014 GP Reference
Orthoebolavirus zairense Variant | Reduced Binding Activity of Atoltivimab Alone | Reduced Binding Activity of Odesivimab Alone | Reduced Binding Activity of Maftivimab Alone | Reduced Binding Activity of INMAZEB
P34S | NC [NC, no change: <5.1-fold reduction in binding activity compared to EBOV Makona 2014 reference GP. A <5.1-fold change in EC50 value is within the inherent variability of this assay. However, the <5.1 fold-change threshold cannot rule out the possibility that substitutions that lead to fold-changes below this threshold have a meaningful impact on binding. The clinical significance of a ≥ 5.1-fold reduction in binding activity is unknown] | NC | NC | NC
N40D | NC | NC | NC | NC
T144M | NC | ≥9-fold [Where an EC50 value could not be accurately calculated, the change in mAb potency in the presence of each mutant was calculated by dividing the maximum antibody concentration tested (333nM) by the EC50 value calculated for atoltivimab, odesivimab, maftivimab, and INMAZEB in the presence of reference VLP] | NC | NC
P209T | NC | NC | NC | NC
Q221K | NC | NC | NC | NC
G224D | NC | ≥9-fold | NC | NC
L239S | NC | NC | NC | NC
K265M | NC | NC | NC | NC
G271E | NC | NC | NC | NC
L273P | NC | NC | NC | NC
I274M | NC | NC | NC | NC
W275L | NC | NC | NC | NC
E280G | >186-fold | Nc | NC | NC
E304A | NC | NC | NC | NC
S347F | NC | NC | NC | NC
R501G | NC | NC | NC | NC
A507S | NC | NC | NC | NC
A507T | NC | NC | NC | NC
I527T | NC | NC | NC | NC
G528R | NC | NC | ≥454-fold | NC
F535L | NC | NC | NC | NC
T544I | NC | NC | NC | NC
H549R | NC | NC | NC | NC
N563T | NC | NC | >454-fold | NC
E564A | NC | NC | NC | NC
E564K | NC | NC | >454-fold | NC
K588N | NC | NC | NC | NC

Neutralization Activity

Neutralization by atoltivimab, maftivimab, and INMAZEB was assessed using VLPs pseudotyped with EBOV Makona 2014 reference GP or variant EBOV GP. Odesivimab did not demonstrate any neutralizing activity in this assay. The results of this assay are shown in Table 8.

Table 8: Summary of Reduced VLP Neutralizing Activities of Atoltivimab, Maftivimab and INMAZEB [A fold reduction in neutralization activity for odesivimab could not be calculated because concentration-dependent activity was not observed within the tested range of concentrations]
Orthoebolavirus zairense Variant | Reduced Neutralizing Activity of Atoltivimab Alone | Reduced Neutralizing Activity of Maftivimab Alone | Reduced Neutralizing Activity of INMAZEB
P34S | NC [NC, no change: <4.3-fold reduction in neutralization activity compared to EBOV Makona 2014 reference GP. A <4.3-fold change in EC50 value is within the inherent variability of this assay. However, the <4.3 fold-change threshold cannot rule out the possibility that substitutions that lead to fold-changes below this threshold have a meaningful impact on neutralization. The clinical significance of a ≥ 4.3-fold reduction in neutralization activity is unknown] | NC | NC
N40D | NC | NC | NC
T144M | NC | NC | NC
P209T | NC | NC | NC
Q221K | NC | NC | NC
G224D | NC | NC | NC
L239S | NC | NC | NC
K265M | >506-fold | NC | NC
G271E | NC | NC | NC
L273P | >506-fold | NC | NC
I274M | NC | NC | NC
W275L | >170-fold [Where an EC50 value could not be accurately calculated, the change in mAb potency in the presence of each mutant was calculated by dividing the maximum antibody concentration tested (66.67nM) by the EC50 value calculated for REGN3470, REGN3471, REGN3479, and REGEN-EB3 in the presence of reference VLP] | NC | NC
E280G | >445-fold | 6-fold | 9-fold
E304A | >506-fold | NC | NC
S347F | NC | NC | NC
R501G | NC | NC | NC
A507S | NC | NC | NC
A507T | NC | NC | NC
I527T | NC | NC | NC
G528R | NC | >81-fold | NC
F535L | NC | NC | NC
T544I | NC | NC | NC
H549R | NC | NC | NC
N563T | NC | >81-fold | NC
E564A | NC | 38-fold | 5-fold
E564K | 5-fold | >451-fold | 6-fold
K588N | NC | NC | NC

Antibody-dependent Cellular Cytotoxicity

The potential to mediate antibody-dependent cellular cytotoxicity (ADCC) was assessed using a surrogate ADCC reporter bioassay measuring FCGR3A signaling. Maftivimab did not demonstrate any ADCC activity in this assay. The results of this assay are shown in Table 9.

Table 9: Summary of Reduced ADCC Activities of Atoltivimab, Odesivimab, and INMAZEB [A fold reduction in ADCC activity for maftivimab and antibody responses to select variants could not be calculated because concentration-dependent activity was not observed within the tested range of concentrations]
Orthoebolavirus zairense Variant | Reduced ADCC Activity of Atoltivimab | Reduced ADCC activity of Odesivimab | Reduced ADCC activity of INMAZEB
P34S | NC [NC, no change: <2.9-fold reduction in ADCC activity compared to EBOV Makona 2014 reference GP. A <2.9-fold change in ADCC activity is within the inherent variability of this assay. However, the <2.9 fold-change threshold cannot rule out the possibility that substitutions that lead to fold-changes below this threshold have a meaningful impact on ADCC activity. The clinical significance of a ≥ 2.9-fold reduction in ADCC activity is unknown] | NC | NC
N40D | NC | NC | NC
T144M | NC | >59-fold [Where an EC50 value could not be accurately calculated, fold change in EC50 in the presence of each mutant was calculated by dividing the maximum antibody concentration tested (100nM) by the EC50 value calculated for REGN3470, REGN3471 with ADCC activity obtained with target cells expressing reference EBOV GP (EBOV Makona 2014)] | NC
P209T | NC | 4-fold | NC
Q221K | NC | 3-fold | NC
G224D | NC | >59-fold | NC
L239S | NC | 5-fold | 3-fold
K265M | 65-fold | 6-fold | 28-fold
G271E | NC | 24-fold | NC
L273P | 10-fold | 6-fold | 19-fold
I274M | NC | NC | 6-fold
W275L | 25-fold | NC | 8-fold
E280G | >237-fold | NC | 6-fold
E304A | NC | NC | NC
S347F | NC | 3-fold | NC
R501G | NC | NC | NC
A507S | NC | 12-fold | NC
A507T | NC | 10-fold | NC
I527T | NC | 6-fold | NC
G528R | NC | NC | NC
F535L | NC | 8-fold | NC
T544I | NC | NC | NC
H549R | NC | 7-fold | 4-fold
N563T | NC | NC | NC
E564A | NC | NC | NC
E564K | NC | NC | NC
K588N | NC | NC | NC

Immune Response

Interaction studies with recombinant live EBOV vaccines and INMAZEB have not been conducted [see Drug Interactions (7.1)].

13 NONCLINICAL TOXICOLOGY

13.1 Carcinogenesis, Mutagenesis, Impairment of Fertility

Carcinogenicity, genotoxicity, and fertility studies have not been conducted with INMAZEB.

14 CLINICAL STUDIES

The efficacy of INMAZEB was evaluated in PALM, a multi-center, open-label, randomized controlled trial sponsored by the National Institute of Allergy and Infectious Diseases (NIAID; NCT03719586). The trial was conducted in the Democratic Republic of Congo, where an outbreak began in August 2018, and enrolled 681 subjects of all ages, including pregnant women, with documented Orthoebolavirus zairense infection and symptoms of any duration who were receiving optimized standard of care (oSOC). Subjects were randomized to receive INMAZEB (50 mg of atoltivimab, 50 mg of maftivimab, and 50 mg of odesivimab per kg) intravenously as a single infusion, an investigational control 50 mg/kg intravenously every third day, for a total of 3 doses, or other investigational drugs. Eligible subjects had a positive reverse transcriptase-polymerase chain reaction (RT-PCR) for the nucleoprotein (NP) gene of Orthoebolavirus zairense and had not received other investigational treatments (with the exception of experimental vaccines) within the previous 30 days. Neonates ≤7 days of age were eligible if the mother had documented infection. Neonates born to a mother who had cleared Orthoebolavirus zairense following a course of her assigned investigational medication were also eligible to be enrolled at investigator discretion regarding the likelihood that the neonate was infected. Randomization was stratified by reverse transcription-PCR cycle threshold calculated using NP targets (CtNP ≤22.0 vs >22.0; corresponding to high and low viral load, respectively) and Ebola Treatment Unit (ETU) site. All subjects received oSOC consisting of a minimum of intravenous fluids, daily clinical laboratory testing, correction of hypoglycemia and electrolyte imbalances, and broad-spectrum antibiotics and antimalarials, as indicated.

The primary efficacy endpoint was 28-day mortality. The primary analysis population includes all subjects who were randomized and concurrently eligible to receive either INMAZEB or the investigational control during the same time period of the trial.

The demographics and baseline characteristics are provided in Table 10 below.

Table 10: Demographics and Baseline Characteristics in PALM Trial
Parameter | INMAZEB (N=154) | Control (N=153)
Mean age (years) | 28 | 31
Age <1 month (%) | 1 (1%) | 2 (1%)
Age 1 month to <1 year (%) | 4 (3%) | 1 (1%)
Age 1 year to < 6 years (%) | 18 (12%) | 13 (8%)
Age 6 years to <12 years (%) | 8 (5%) | 4 (3%)
Age 12 years to <18 years (%) | 8 (5%) | 8 (5%)
Age 18 years to <50 years (%) | 93 (60%) | 105 (69%)
Age 50 years to <65 years (%) | 17 (11%) | 18 (12%)
Age ≥65 years (%) | 5 (3%) | 2 (1%)
Female (%) | 90 (58%) | 80 (52%)
Positive result on pregnancy test [Pregnancy positive test was calculated based on subjects who had pregnancy test result.] , n (%) | 2/67 (3%) | 4/61 (7%)
RT-PCR CtNP cycle threshold ≤22, n | 66 | 64
Median RT-PCR CtNP (IQR) | 22.7 (20.1, 28.1) | 22.9 (18.8, 26.4)
Median creatinine (IQR) | 1.0 (0.7, 4.0) | 1.1 (0.7, 3.2)
Median AST (IQR) | 225.5 (98.0, 941.0) | 351.0 (109, 1404.0)
Median ALT (IQR) | 165.0 (56.0, 418.0) | 223.5 (47.0, 564.0)
Median days from onset of symptoms to randomization (IQR) | 5.0 (3.0, 7.0) | 5.0 (3.0, 7.0)
Reported Vaccination with rVSV-ZEBOV vaccine, n (%) | 34 (22%) | 41 (27%)
<10 days before ETU admission | 20/34 (59%) | 21/41 (51%)
≥10 days before ETU admission | 14/34 (41%) | 18/41 (44%)
Timing unknown | 0/34 (0%) | 2/41 (5%)
CtNP = cycle threshold calculated using NP targets; IQR = interquartile range; AST=Aspartate aminotransferase; ALT=Alanine aminotransferase; ETU=Ebola treatment unit

The PALM trial was stopped early on the basis of a pre-specified interim analysis showing a statistically significant reduction in mortality for INMAZEB compared to control.

Mortality efficacy results are shown in Table 11.

Table 11: Mortality Rates in PALM Trial
Efficacy Endpoints | INMAZEB [Both INMAZEB and Control were administered with optimized standard of care] (N=154) | Control (N=153)
Overall
28-day mortality, n (%) | 52 (34%) | 78 (51%)
Mortality rate difference relative to control (95% CI) | -17.2 (-28.4, -2.6)
p-Value [The result is significant according to the interim stopping boundary, p<0.028] | 0.0024
Baseline Viral Load
High viral load (CtNP ≤ 22) [Cepheid GeneXpert Ebola® Assay used for detection of Orthoebolavirus zairense RNA] | n=66 | n=64
28-day mortality, n (%) | 42 (64%) | 56 (88%)
Mortality rate difference relative to control (95% CI) | -23.9 (-43.8, -6.4)
Low viral load (CtNP > 22) | n=88 | n=88
28-day mortality, n (%) | 10 (11%) | 22 (25%)
Mortality rate difference relative to control (95% CI) | -13.6 (-31.8, -1.4)
Age group
Adults (age ≥18 years) | 39/115 (34%) | 67/125 (54%)
12 to < 18 years of age | 2/8 (25%) | 4/8 (50%)
6 to < 12 years of age | 1/8 (13%) | 1/4 (25%)
< 6 years of age | 10/23 (43%) | 6/16 (38%)
Sex
Male | 21/64 (33%) | 31/73 (42%)
Female | 31/90 (34%) | 47/80 (59%)

Figure 1: Kaplan-Meier Curve for Overall Mortality

16 HOW SUPPLIED/STORAGE AND HANDLING

INMAZEB (atoltivimab, maftivimab, and odesivimab-ebgn) injection is a clear to slightly opalescent and colorless to pale yellow solution. It is supplied in a carton containing one single dose vial of:

- 241.7 mg of atoltivimab, 241.7 mg of maftivimab, and 241.7 mg of odesivimab per 14.5 mL (16.67 mg/16.67 mg/16.67 mg per mL) (NDC 61755-018-01)
- 483.3 mg of atoltivimab, 483.3 mg of maftivimab, and 483.3 mg of odesivimab per 14.5 mL (33.33 mg/33.33 mg/33.33 mg per mL) (NDC 61755-019-01)

STORAGE AND HANDLING

Prior to dilution

Store INMAZEB vial refrigerated at 2°C to 8°C (36°F to 46°F) in the original carton to protect from light. Do not freeze or shake.

STORAGE AND HANDLING

After dilution

INMAZEB does not contain preservatives. It is always recommended to administer intravenous medication immediately after preparation when possible. Store the diluted INMAZEB solution as specified according to Table 12 below. Do not freeze the diluted solution [see Dosage and Administration (2.2)].

Table 12: Diluted INMAZEB Solution Storage Conditions
Diluent Used to Prepare Solution for Infusion | Diluted INMAZEB Solution Storage Conditions
0.9% Sodium Chloride Injection, USP | Store at room temperature up to 25°C (77°F) for no more than 8 hours or refrigerated at 2°C to 8°C (36°F to 46°F) for no more than 24 hours.
5% Dextrose Injection, USP | Store at room temperature up to 25°C (77°F) for no more than 4 hours or refrigerated at 2°C to 8°C (36°F to 46°F) for no more than 24 hours.
Lactated Ringer's Injection, USP | Store at room temperature up to 25°C (77°F) for no more than 4 hours or refrigerated at 2°C to 8°C (36°F to 46°F) for no more than 4 hours.

17 PATIENT COUNSELING INFORMATION

Hypersensitivity Reactions Including Infusion-Associated Events

Inform patients that hypersensitivity reactions including infusion-associated events have been reported during and post-infusion with INMAZEB and to immediately report if they experience any symptoms of systemic hypersensitivity reactions [see Warnings and Precautions (5.1)].

Lactation

Instruct patients with Orthoebolavirus zairense infection not to breastfeed because of the risk of passing Orthoebolavirus zairense to the baby [see Use in Specific Populations (8.2)].

Manufactured by:
Regeneron Pharmaceuticals, Inc.
777 Old Saw Mill River Road
Tarrytown, NY 10591-6707
U.S. License No. 1760
INMAZEB is a registered trademark owned by Regeneron Pharmaceuticals, Inc.
©2024 Regeneron Pharmaceuticals, Inc. All rights reserved.

PRINCIPAL DISPLAY PANEL - 14.5 mL Vial Carton - 61755-018

NDC 61755-018-01
Rx only

Inmazeb®
(atoltivimab, maftivimab,
and odesivimab – ebgn)
Injection

241.7 mg / 241.7 mg / 241.7 mg per 14.5 mL
(16.67 mg / 16.67 mg / 16.67 mg per mL)

For Intravenous Infusion after Dilution

Single-Dose Vial

Discard unused portion.

Do not use vial if seal is broken or missing.

One 14.5 mL Vial

PRINCIPAL DISPLAY PANEL - 14.5 mL Vial Carton - 61755-019

NDC 61755-019-01
Rx only

Inmazeb®
(atoltivimab, maftivimab,
and odesivimab – ebgn)
Injection

483.3 mg / 483.3 mg / 483.3 mg per 14.5 mL
(33.33 mg / 33.33 mg / 33.33 mg per mL)

For Intravenous Infusion after Dilution

Single-Dose Vial

Discard unused portion.

Do not use vial if seal is broken or missing.

One 14.5 mL Vial